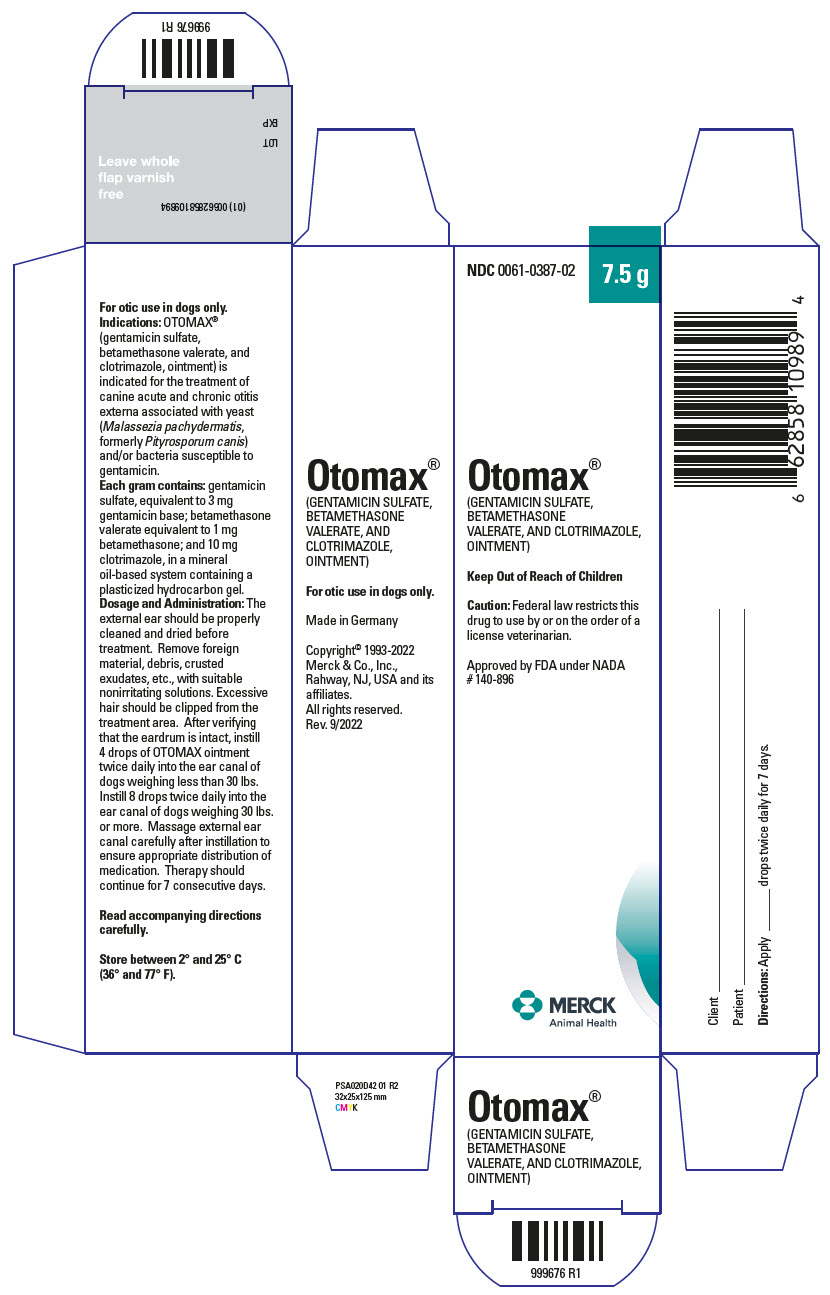 DRUG LABEL: Otomax
NDC: 0061-0387 | Form: OINTMENT
Manufacturer: Merck Sharp & Dohme Corp.
Category: animal | Type: PRESCRIPTION ANIMAL DRUG LABEL
Date: 20251113

ACTIVE INGREDIENTS: GENTAMICIN SULFATE 3 mg/1 g; BETAMETHASONE VALERATE 1 mg/1 g; CLOTRIMAZOLE 10 mg/1 g

Otomax®
(GENTAMICIN SULFATE, BETAMETHASONE VALERATE AND CLOTRIMAZOLE, OINTMENT)

Approved by FDA under NADA # 140-896

PRODUCT INFORMATION

VETERINARY

For Otic Use in Dogs Only

CAUTION: Federal law restricts this drug to use by or on the order of a licensed veterinarian. Keep this and all drugs out of the reach of children.

DESCRIPTION

DESCRIPTION Each gram of OTOMAX ointment contains gentamicin sulfate, equivalent to 3 mg gentamicin base; betamethasone valerate, equivalent to 1 mg betamethasone; and 10 mg clotrimazole, in a mineral oil-based system containing a plasticized hydrocarbon gel.

PHARMACOLOGY

Gentamicin: Gentamicin sulfate is an aminoglycoside antibiotic active against a wide variety of pathogenic gram-negative and gram-positive bacteria. In vitro tests have determined that gentamicin is bactericidal and acts by inhibiting normal protein synthesis in susceptible microorganisms. Specifically, gentamicin is active against the following organisms commonly isolated from canine ears: Staphylococcus aureus, other Staphylococcus spp., Pseudomonas aeruginosa, Proteus spp., and Escherichia coli.

Betamethasone: Betamethasone valerate is a synthetic adrenocorticoid for dermatologic use. Betamethasone, an analog of prednisolone, has a high degree of corticosteroid activity and a slight degree of mineralocorticosteroid activity. Betamethasone valerate, the 17-valerate ester of betamethasone, has been shown to provide anti-inflammatory and antipruritic activity in the topical management of corticosteroid-responsive otitis externa.

Topical corticosteroids can be absorbed from normal, intact skin. Inflammation can increase percutaneous absorption. Once absorbed through the skin, topical corticosteroids are handled through pharmacokinetic pathways similar to systemically administered corticosteroids.

Clotrimazole: Clotrimazole is a broad-spectrum antifungal agent that is used for the treatment of dermal infections caused by various species of pathogenic dermatophytes and yeasts. The primary action of clotrimazole is against dividing and growing organisms.

In vitro, clotrimazole exhibits fungistatic and fungicidal activity against isolates of Trichophyton rubrum, Trichophyton mentagrophytes, Epidermophyton floccosum, Microsporum canis, Candida spp., and Malassezia pachydermatis (Pityrosporum canis). Resistance to clotrimazole is very rare among the fungi that cause superficial mycoses.

In an induced otitis externa infected with Malassezia pachydermatis, 1% clotrimazole in the OTOMAX vehicle was effective both microbiologically and clinically in terms of reduction of exudate, odor, and swelling.

In studies of the mechanism of action, the minimum fungicidal concentration of clotrimazole caused leakage of intra-cellular phosphorus compounds into the ambient medium with concomitant breakdown of cellular nucleic acids and accelerated potassium efflux. These events began rapidly and extensively after addition of the drug.

Clotrimazole is very poorly absorbed following dermal application.

Gentamicin-Betamethasone-Clotrimazole: By virtue of its three active ingredients, OTOMAX ointment has antibacterial, anti-inflammatory, and antifungal activity.

In component efficacy studies, the compatibility and additive effect of each of the components were demonstrated. In clinical field trials, OTOMAX ointment was effective in the treatment of otitis externa associated with bacteria and Malassezia pachydermatis. OTOMAX ointment reduced discomfort, redness, swelling, exudate, and odor, and exerted a strong antimicrobial effect.

VETERINARY INDICATIONS

INDICATIONS OTOMAX ointment is indicated for the treatment of canine acute and chronic otitis externa associated with yeast (Malassezia pachydermatis, formerly Pityrosporum canis) and/or bacteria susceptible to gentamicin.

CONTRAINDICATIONS

CONTRAINDICATIONS If hypersensitivity to any of the components occurs, treatment should be discontinued and appropriate therapy instituted. Concomitant use of drugs known to induce ototoxicity should be avoided. Do not use in dogs with known perforation of eardrums.

WARNINGS

WARNINGS The use of OTOMAX ointment has been associated with deafness or partial hearing loss in a small number of sensitive dogs (eg, geriatric). The hearing deficit is usually temporary. If hearing or vestibular dysfunction is noted during the course of treatment, discontinue use of OTOMAX ointment immediately and flush the ear canal thoroughly with a nonototoxic solution.

Corticosteroids administered to dogs, rabbits, and rodents during pregnancy have resulted in cleft palate in offspring. Other congenital anomalies including deformed forelegs, phocomelia, and anasarca have been reported in offspring of dogs which received corticosteroids during pregnancy.

Clinical and experimental data have demonstrated that corticosteroids administered orally or parenterally to animals may induce the first stage of parturition if used during the last trimester of pregnancy and may precipitate premature parturition followed by dystocia, fetal death, retained placenta, and metritis.

PRECAUTIONS

PRECAUTIONS Identification of infecting organisms should be made either by microscopic roll smear evaluation or by culture as appropriate. Antibiotic susceptibility of the pathogenic organism(s) should be determined prior to use of this preparation.

If overgrowth of nonsusceptible bacteria, fungi, or yeasts occur, or if hypersensitivity develops, treatment should be discontinued and appropriate therapy instituted.

Administration of recommended doses of OTOMAX ointment beyond 7 days may result in delayed wound healing. Avoid ingestion. Adverse systemic reactions have been observed following the oral ingestion of some topical corticosteroid preparations. Patients should be closely observed for the usual signs of adrenocorticoid overdosage which include sodium retention, potassium loss, fluid retention, weight gain, polydipsia, and/or polyuria. Prolonged use or overdosage may produce adverse immunosuppressive effects.

Use of corticosteroids, depending on dose, duration, and specific steroid, may result in endogenous steroid production inhibition following drug withdrawal. In patients presently receiving or recently withdrawn from corticosteroid treatments, therapy with a rapidly-acting corticosteroid should be considered in especially stressful situations. Before instilling any medication into the ear, examine the external ear canal thoroughly to be certain the tympanic membrane is not ruptured in order to avoid the possibility of transmitting infection to the middle ear as well as damaging the cochlea or vestibular apparatus from prolonged contact.

ANIMAL PHARMACOLOGY AND OR TOXICOLOGY

TOXICOLOGY Clinical and safety studies with OTOMAX ointment have shown a wide safety margin at the recommended dose level in dogs (see PRECAUTIONS/SIDE EFFECTS).

SIDE EFFECTS

Gentamicin: While aminoglycosides are absorbed poorly from skin, intoxication may occur when aminoglycosides are applied topically for prolonged periods of time to large wounds, burns, or any denuded skin, particularly if there is renal insufficiency. All aminoglycosides have the potential to produce reversible and irreversible vestibular, cochlear, and renal toxicity.

Betamethasone: Side effects such as SAP and SGPT enzyme elevations, weight loss, anorexia, polydipsia, and polyuria have occurred following the use of parenteral or systemic synthetic corticosteroids in dogs. Vomiting and diarrhea (occasionally bloody) have been observed in dogs and cats.

Cushing's syndrome in dogs has been reported in association with prolonged or repeated steroid therapy.

Clotrimazole: The following have been reported occasionally in humans in connection with the use of clotrimazole: erythema, stinging, blistering, peeling, edema, pruritus, urticaria, and general irritation of the skin not present before therapy.

DOSAGE AND ADMINISTRATION The external ear should be thoroughly cleaned and dried before treatment. Remove foreign material, debris, crusted exudates, etc., with suitable nonirritating solutions. Excessive hair should be clipped from the treatment area. After verifying that the eardrum is intact, instill 4 drops from the 7.5 g and 15 g tube, and 15 g and 30 g bottle (2 drops from the 215 g bottle) of OTOMAX ointment twice daily into the ear canal of dogs weighing less than 30 lbs. Instill 8 drops from the 7.5 g and 15 g tube, and 15 g and 30 g bottle (4 drops from the 215 g bottle) twice daily into the ear canal of dogs weighing 30 lbs or more. Massage external ear canal carefully after instillation to ensure appropriate distribution of medication. Therapy should continue for 7 consecutive days.

HOW SUPPLIED

HOW SUPPLIED OTOMAX ointment is available in 7.5 g and 15 g tubes as well as in 215 g, 30 g, and 15 g plastic bottles.

STORAGE AND HANDLING

Store between 2°and 25°C (36° and 77°F). Shake well before use when using the 215 g bottle, 30g bottle, and 15 g bottle.

Made in Germany

Intervet Inc. d/b/a Merck Animal Health, Madison, NJ 07940

Copyright ® 1993-2022 Merck & Co., Inc., Rahway, NJ, US and it's affiliates. All rights reserved.
Rev. 9/2022

397831 R1

PRINCIPAL DISPLAY PANEL - 7.5 g Tube Carton

NDC 0061-0387-02

7.5 g

Otomax®
(GENTAMICIN SULFATE,
BETAMETHASONE
VALERATE, AND CLOTRIMAZOLE,
OINTMENT)

Keep Out of Reach of Children

Caution: Federal law restricts this
drug to use by or on the order of a
license veterinarian.

Approved by FDA under NADA
# 140-896

MERCK
Animal Health